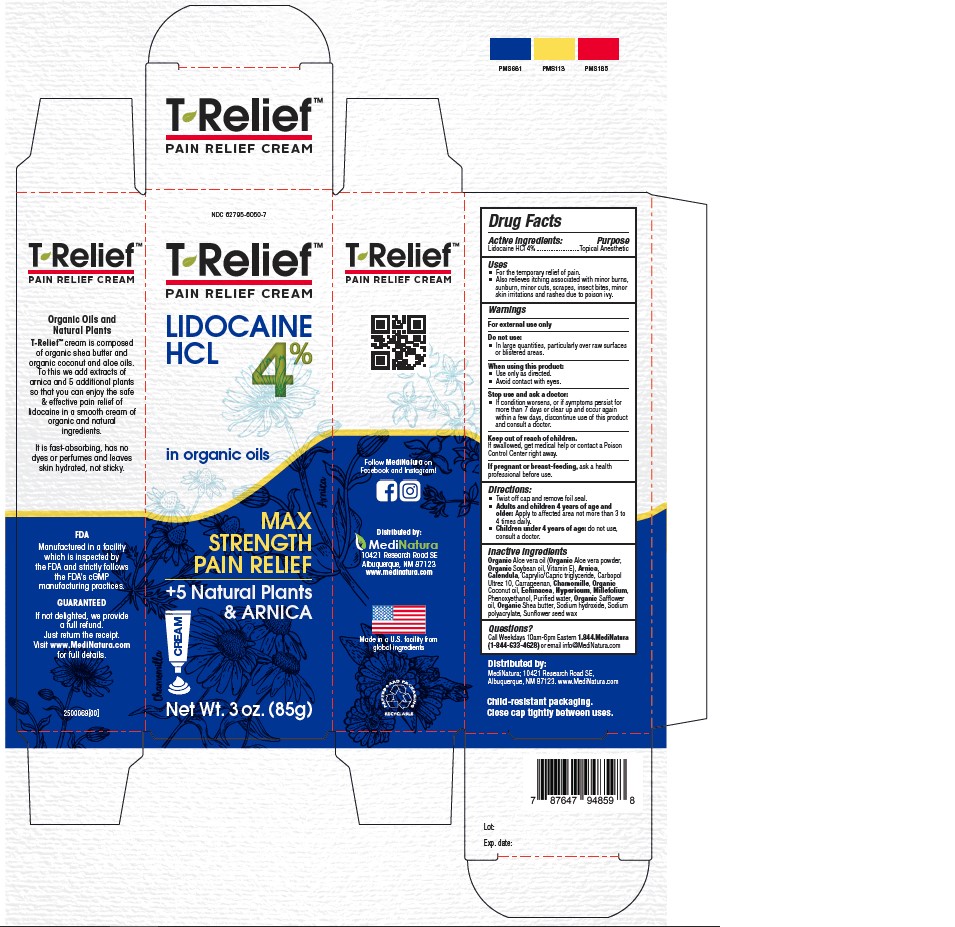 DRUG LABEL: T-Relief Lidocaine HCL 4%
NDC: 62795-6050 | Form: CREAM
Manufacturer: Medinatura New Mexico Inc.
Category: otc | Type: HUMAN OTC DRUG LABEL
Date: 20251211

ACTIVE INGREDIENTS: LIDOCAINE HYDROCHLORIDE 3.4 g/85 g
INACTIVE INGREDIENTS: SAFFLOWER OIL 0.17 g/85 g; CHONDRUS CRISPUS 0.0026 g/85 g; HYPERICUM PERFORATUM WHOLE 0.000102 g/85 g; ALOE VERA LEAF 0.0000023 g/85 g; SOYBEAN OIL 0.0002 g/85 g; MATRICARIA CHAMOMILLA 0.077 g/85 g; SODIUM POLYACRYLATE (8000 MW) 0.00086 g/85 g; ARNICA MONTANA 0.0036 g/85 g; CAPRYLIC/CAPRIC TRIGLYCERIDE 0.425 g/85 g; PHENOXYETHANOL 0.425 g/85 g; ACHILLEA MILLEFOLIUM WHOLE 0.23 g/85 g; TOCOPHEROL 0.0000001 g/85 g; SHEA BUTTER 4.25 g/85 g; POLYACRYLIC ACID (800000 MW) 0.51 g/85 g; COCONUT OIL 4.25 g/85 g; WATER 67.4 g/85 g; SODIUM HYDROXIDE 0.128 g/85 g; HELIANTHUS ANNUUS (SUNFLOWER) SEED WAX 0.25 g/85 g; ECHINACEA, UNSPECIFIED 0.638 g/85 g

Active ingredients: Purpose
Lidocaine HCl 4% .........................Topical Anesthetic

Stop use and ask a doctor:
If condition worsens, or if symptoms persist for more than 7 days or clear up and occur again within a few days, discontinue use of this product and consult a doctor.

Do not use:
In large quantities, particularly over raw surfaces or blistered areas.

Keep out of reach of children.
If swallowed, get medical help or contact a Poison
Control Center right away.

If pregnant or breast-feeding, ask a health
professional before use.

Uses
For the temporary relief of pain. Also relieves itching associated with minor burns, sunburn, minor cuts, scrapes, insect bites, minor
skin irritations and rashes due to poison ivy.

Questions?

Call Weekdays 10am-6pm Eastern 1.844.MediNatura (1-844-633-4628) or email info@MediNatura.com

When using this product:
Use only as directed.
Avoid contact with eyes.

WARNINGS

For external use only

Directions:
Twist off cap and remove foil seal.
Adults and children 4 years of age and
older: Apply to affected area not more than 3 to
4 times daily.
Children under 4 years of age: do not use,
consult a doctor.

Inactive ingredients
Organic Aloe vera oil (Organic Aloe vera powder,
Organic Soybean oil, Vitamin E), Arnica,
Calendula, Caprylic/Capric triglyceride, Carbopol
Ultrez 10, Carrageenan, Chamomille, Organic
Coconut oil, Echinacea, Hypericum, Millefolium,
Phenoxyethanol, Purified water, Organic Safflowe
oil, Organic Shea butter, Sodium hydroxide, Sodium
polyacrylate, Sunflower seed wax

INDICATIONS AND USAGE

- For the temporary relief of pain.
- Also relieves itching associated with minor burns, sunburn, minor cuts, scrapes, inspect bites, minor skin irritations and rashes due to poison ivy.

INDICATIONS AND USAGE

- For the temporary relief of pain.
- Also relieves itching associated with minor burns, sunburn, minor cuts, scrapes, insect bites, minor skin irritations and rashes due to poison ivy.